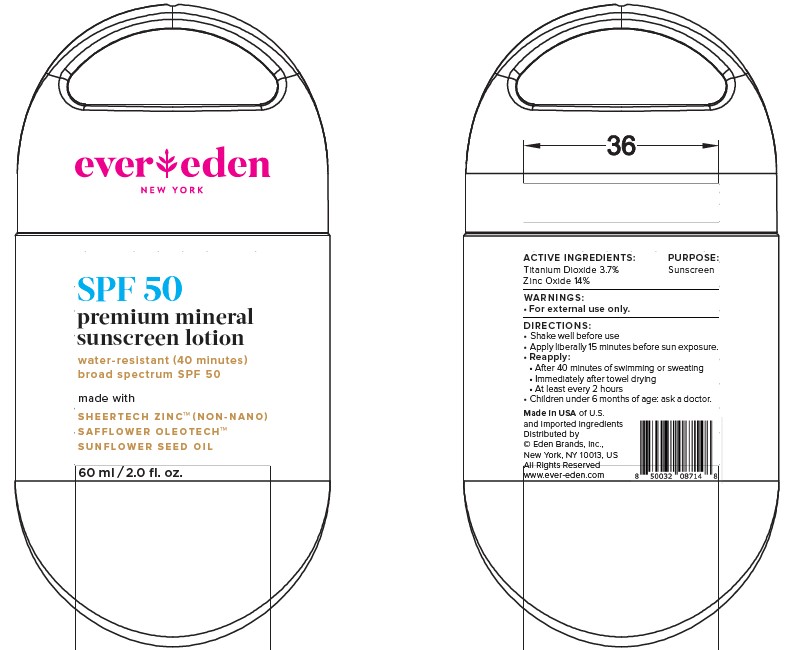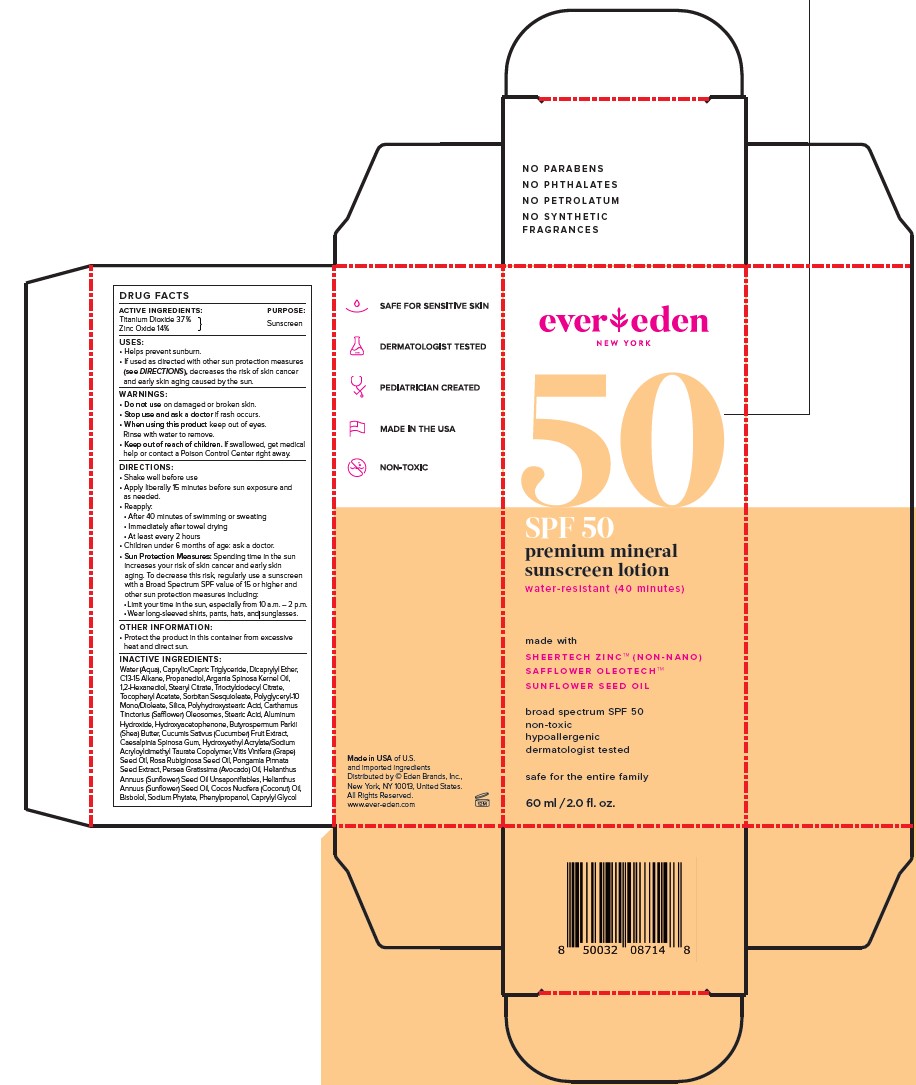 DRUG LABEL: Evereden SPF50 Premium Mineral Sunscreen
NDC: 72113-107 | Form: LOTION
Manufacturer: Eden Brands Inc
Category: otc | Type: HUMAN OTC DRUG LABEL
Date: 20231016

ACTIVE INGREDIENTS: ZINC OXIDE 14 g/100 mL; TITANIUM DIOXIDE 3.7 g/100 mL
INACTIVE INGREDIENTS: SUNFLOWER OIL; POLYHYDROXYSTEARIC ACID (2300 MW); 1,2-HEXANEDIOL; SORBITAN SESQUIOLEATE; POLYGLYCERYL-10 DIOLEATE; PONGAMIA PINNATA SEED; AVOCADO OIL; CUCUMBER; CAESALPINIA SPINOSA RESIN; ROSA RUBIGINOSA SEED OIL; GRAPE SEED OIL; HYDROXYACETOPHENONE; SHEA BUTTER; PHYTATE SODIUM; PHENYLPROPANOL; CAPRYLYL GLYCOL; MEDIUM-CHAIN TRIGLYCERIDES; DICAPRYLYL ETHER; ARGAN OIL; ALPHA-TOCOPHEROL ACETATE; SILICON DIOXIDE; CARTHAMUS TINCTORIUS (SAFFLOWER) OLEOSOMES; STEARIC ACID; ALUMINUM HYDROXIDE; C13-15 ALKANE; MONOSTEARYL CITRATE; HYDROXYETHYL ACRYLATE/SODIUM ACRYLOYLDIMETHYL TAURATE COPOLYMER (45000 MPA.S AT 1%); COCONUT OIL; LEVOMENOL; WATER; PROPANEDIOL; TRIOCTYLDODECYL CITRATE

SPF50 Premium Mineral Sunscreen Lotion

ACTIVE INGREDIENT

Titanium Dioxide 3.7%, Zinc Oxide 14%

PURPOSE

Sunscreen

USES

- Helps prevent sunburn.
- If used as directed with other sun protection measures (see Directions), decreases the risk of skin cancer and early skin aging caused by the sun.

WARNINGS

For external use only.
Do not use on damaged or broken skin.
Stop use and ask a doctor if rash occurs.
When using this product keep out of eyes. Rinse with water to remove.

WARNINGS

Keep out of reach of children. If swallowed, get medical help or contact a Poison Control Center right away.

DIRECTIONS

• Shake well before use
• Apply liberally 15 minutes before sun exposure and
as needed.
• Reapply:
• After 40 minutes of swimming or sweating
• Immediately after towel drying
• At least every 2 hours
• Children under 6 months of age: ask a doctor.
• Sun Protection Measures: Spending time in the sun increases your risk of skin cancer and early skin aging. To decrease this risk, regularly use a sunscreen with a Broad Spectrum SPF value of 15 or higher and other sun protection measures including:

• Limit your time in the sun, especially from 10 a.m. – 2 p.m.
• Wear long-sleeved shirts, pants, hats, and sunglasses.

INACTIVE INGREDIENTS

Water (Aqua), Caprylic/Capric Triglyceride, Dicaprylyl Ether, C13-15 Alkane, Propanediol, Argania Spinosa Kernel Oil, 1,2-Hexanediol, Stearyl Citrate, Trioctyldodecyl Citrate, Tocopheryl Acetate, Sorbitan Sesquioleate, Polyglyceryl-10 Mono/Dioleate, Silica, Polyhydroxystearic Acid, Carthamus Tinctorius (Safflower) Oleosomes, Stearic Acid, Aluminum Hydroxide, Hydroxyacetophenone, Butyrospermum Parkii (Shea) Butter, Cucumis Sativus (Cucumber) Fruit Extract, Caesalpinia Spinosa Gum, Hydroxyethyl Acrylate/Sodium Acryloyldimethyl Taurate Copolymer, Vitis Vinifera (Grape) Seed Oil, Rosa Rubiginosa Seed Oil, Pongamia Pinnata Seed Extract, Persea Gratissima (Avocado) Oil, Helianthus Annuus (Sunflower) Seed Oil Unsaponifiables, Helianthus Annuus (Sunflower) Seed Oil, Cocos Nucifera (Coconut) Oil, Bisbolol, Sodium Phytate, Phenylpropanol, Caprylyl Glycol